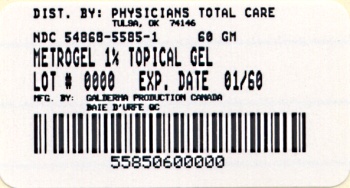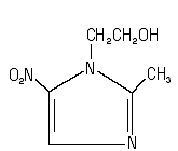 DRUG LABEL: METROGEL
NDC: 54868-5585 | Form: GEL
Manufacturer: Physicians Total Care, Inc.
Category: prescription | Type: HUMAN PRESCRIPTION DRUG LABEL
Date: 20120207

ACTIVE INGREDIENTS: METRONIDAZOLE 10 mg/1 g
INACTIVE INGREDIENTS: betadex; edetate disodium; methylparaben; niacinamide; phenoxyethanol; propylene glycol; propylparaben; water

HIGHLIGHTS OF PRESCRIBING INFORMATION

These highlights do not include all the information needed to use METROGEL (metronidazole) Gel, 1% safely and effectively. See full prescribing information for METROGEL (metronidazole) Gel, 1% METROGEL® (metronidazole) Gel, 1% For topical use only. Initial U.S. Approval 1963

1 INDICATIONS AND USAGE

METROGEL® (metronidazole) Gel, 1% is a nitroimidazole indicated for the topical treatment of inflammatory lesions of rosacea. (1)

2 DOSAGE AND ADMINISTRATION

- Not for oral, ophthalmic or intravaginal use. (2)
- Apply and rub in a thin film of METROGEL once daily to affected area(s). (2)
- Treated areas should be cleansed before the application of METROGEL. (2)
- Cosmetics may be applied after the application of METROGEL. (2)

3 DOSAGE FORMS AND STRENGTHS

Gel, 1%.

4 CONTRAINDICATIONS

METROGEL is contraindicated in those patients with a history of hypersensitivity to metronidazole or to any other ingredient in this formulation. (4)

5 WARNINGS AND PRECAUTIONS

- Peripheral neuropathy, characterized by numbness or paresthesia of an extremity has been reported in patients treated with systemic metronidazole. Although not evident in clinical trials for topical metronidazole, peripheral neuropathy has been reported with the post approval use. The appearance of abnormal neurologic signs should prompt immediate reevaluation of METROGEL therapy. (5.1)
- Metronidazole is a nitroimidazole and should be used with care in patients with evidence of, or history of, blood dyscrasia. (5.2)
- If dermatitis occurs, patients may need to discontinue use. (5.3)
- Topical metronidazole has been reported to cause tearing of the eyes. Therefore, contact with the eyes should be avoided. (5.4)

6 ADVERSE REACTIONS

Most common adverse reactions (incidence > 2%) are nasopharyngitis, upper respiratory tract infection, and headache. (6)

To report SUSPECTED ADVERSE REACTIONS, contact Galderma Laboratories, L.P. at 1-866-735-4137, or FDA at 1-800-FDA-1088 or www.fda.gov/medwatch

7 DRUG INTERACTIONS

Oral metronidazole has been reported to potentiate the anticoagulant effect of coumarin and warfarin, resulting in a prolongation of prothrombin time. Drug interactions should be kept in mind when METROGEL is prescribed for patients who are receiving anticoagulant treatment, although they are less likely to occur with topical metronidazole administration because of low absorption. (7)

FULL PRESCRIBING INFORMATION

1 INDICATIONS AND USAGE

METROGEL® is indicated for the topical treatment of inflammatory lesions of rosacea.

2 DOSAGE AND ADMINISTRATION

Apply and rub in a thin film of METROGEL once daily to affected area(s).

A gentle cleanser should be used before the application of METROGEL.

Cosmetics may be applied after the application of METROGEL.

Not for oral, ophthalmic or intravaginal use.

3 DOSAGE FORMS AND STRENGTHS

Gel, 1%. METROGEL is a clear, colorless to pale yellow gel. Each gram of METROGEL contains 10mg (1%) of metronidazole.

4 CONTRAINDICATIONS

METROGEL is contraindicated in patients with a history of hypersensitivity to metronidazole or to any other ingredient in the formulation.

5 WARNINGS AND PRECAUTIONS

5.1 Neurologic Disease

Peripheral neuropathy, characterized by numbness or paresthesia of an extremity has been reported in patients treated with systemic metronidazole. Although not evident in clinical trials for topical metronidazole, peripheral neuropathy has been reported with the post approval use. The appearance of abnormal neurologic signs should prompt immediate reevaluation of METROGEL therapy. Metronidazole should be administered with caution to patients with central nervous system diseases.

5.2 Blood Dyscrasias

Metronidazole is a nitroimidazole; use with care in patients with evidence of, or history of, blood dyscrasia.

5.3 Contact Dermatitis

Irritant and allergic contact dermatitis have been reported. If dermatitis occurs, patients may need to discontinue use.

5.4 Eye Irritation

Topical metronidazole has been reported to cause tearing of the eyes. Avoid contact with the eyes.

6 ADVERSE REACTIONS

6.1 Clinical Trials Experience

Because clinical trials are conducted under widely varying conditions, adverse reaction rates observed in the clinical trials of a drug cannot be directly compared to rates in the clinical trials of another drug and may not reflect the rates observed in practice.
In a controlled clinical trial, 557 patients used metronidazole gel, 1% and 189 patients used the gel vehicle once daily for up to 10 weeks. The following table summarizes selected adverse reactions that occurred at a rate of ≥1%:

Table 1: Adverse Reactions That Occurred at a Rate of ≥1%
System Organ Class/Preferred Term | Metronidazole Gel, 1% | Gel Vehicle
 | N= 557 | N= 189
Patients with at least one AE Number (%) of Patients | 186 (33.4) | 51 (27.0)
Infections and infestations | 76 (13.6) | 28 (14.8)
Bronchitis | 6 (1.1) | 3 (1.6)
Influenza | 8 (1.4) | 1 (0.5)
Nasopharyngitis | 17 (3.1) | 8 (4.2)
Sinusitis | 8 (1.4) | 3 (1.6)
Upper respiratory tract infection | 14 (2.5) | 4 (2.1)
Urinary tract infection | 6 (1.1) | 1 (0.5)
Vaginal mycosis | 1 (0.2) | 2 (1.1)
Musculoskeletal and connective tissue disorders | 19 (3.4) | 5 (2.6)
Back pain | 3 (0.5) | 2 (1.1)
Neoplasms | 4 (0.7) | 2 (1.1)
Basal cell carcinoma | 1 (0.2) | 2 (1.1)
Nervous system disorders | 18 (3.2) | 3 (1.6)
Headache | 12 (2.2) | 1 (0.5)
Respiratory, thoracic and mediastinal disorders | 22 (3.9) | 5 (2.6)
Nasal congestion | 6 (1.1) | 3 (1.6)
Skin and subcutaneous tissue disorders | 36 (6.5) | 12 (6.3)
Contact dermatitis | 7 (1.3) | 1 (0.5)
Dry skin | 6 (1.1) | 3 (1.6)
Vascular disorders | 8 (1.4) | 1 (0.5)
Hypertension | 6 (1.1) | 1 (0.5)

Table 2: Local Cutaneous Signs and Symptoms of Irritation That Were Worse Than Baseline
 | Metronidazole Gel, 1% | Gel Vehicle
Sign/Symptom | N= 544 | N= 184
Dryness | 138 (25.4) | 63 (34.2)
Mild | 93 (17.1) | 41 (22.3)
Moderate | 42 (7.7) | 20 (10.9)
Severe | 3 (0.6) | 2 (1.1)
Scaling | 134 (24.6) | 60 (32.6)
Mild | 88 (16.2) | 32 (17.4)
Moderate | 43 (7.9) | 27 (14.7)
Severe | 3 (0.6) | 1 (0.5)
Pruritus | 86 (15.8) | 35 (19.0)
Mild | 53 (9.7) | 21 (11.4)
Moderate | 27 (5.0) | 13 (7.1)
Severe | 6 (1.1) | 1 (0.5)
Stinging/burning | 56 (10.3) | 28 (15.2)
Mild | 39 (7.2) | 18 (9.8)
Moderate | 7 (1.3) | 9 (4.9)
Severe | 10 (1.8) | 1 (0.5)

The following additional adverse experiences have been reported with the topical use of metronidazole: skin irritation, transient redness, metallic taste, tingling or numbness of extremities, and nausea.

6.2 Post Marketing Experience

The following adverse reaction has been identified during post approval use of topical metronidazole: peripheral neuropathy. Because this reaction is reported voluntarily from a population of uncertain size, it is not always possible to reliably estimate the frequency or establish a causal relationship to drug exposure.

7 DRUG INTERACTIONS

Oral metronidazole has been reported to potentiate the anticoagulant effect of coumarin and warfarin, resulting in a prolongation of prothrombin time. Drug interactions should be kept in mind when METROGEL is prescribed for patients who are receiving anticoagulant treatment, although they are less likely to occur with topical metronidazole administration because of low absorption.

8 USE IN SPECIFIC POPULATIONS

8.1 Pregnancy

Teratogenic Effects: Pregnancy Category B.
There are no adequate and well-controlled studies with the use of METROGEL in pregnant women.
Metronidazole crosses the placental barrier and enters the fetal circulation rapidly. No fetotoxicity was observed after oral administration of metronidazole in rats or mice at 200 and 20 times, respectively, the expected clinical dose. However, oral metronidazole has shown carcinogenic activity in rodents. Because animal reproduction studies are not always predictive of human response, METROGEL should be used during pregnancy only if clearly needed.

8.3 Nursing Mothers

After oral administration, metronidazole is secreted in breast milk in concentrations similar to those found in the plasma. Even though blood levels taken after topical metronidazole application are significantly lower than those achieved after oral metronidazole a decision should be made whether to discontinue nursing or to discontinue the drug, taking into account the importance of the drug to the mother and the risk to the infant.

8.4 Pediatric Use

Safety and effectiveness in pediatric patients have not been established.

8.5 Geriatric Use

Sixty-six subjects aged 65 years and older were treated with metronidazole gel, 1% in the clinical study. No overall differences in safety or effectiveness were observed between these subjects and younger subjects, and other reported clinical experience has not identified differences in responses between the elderly and younger patients, but greater sensitivity of some older individuals cannot be ruled out.

10 OVERDOSAGE

There are no reported human experiences with overdosage of METROGEL. Topically applied metronidazole can be absorbed in sufficient amount to produce systemic effects.

11 DESCRIPTION

METROGEL (metronidazole) Gel, 1% contains metronidazole, USP. Chemically, metronidazole is 2-methyl-5-nitro-1 H-imidazole-1-ethanol. The molecular formula for metronidazole is C6H9N3O3. It has the following structural formula:

Metronidazole has a molecular weight of 171.16. It is a white to pale yellow crystalline powder. It is slightly soluble in alcohol and has solubility in water of 10 mg/mL at 20˚C. Metronidazole belongs to the nitroimidazole class of compounds.
METROGEL is a clear, colorless to pale yellow, aqueous gel; each gram contains 10 mg of metronidazole in a base of betadex, edetate disodium, hydroxyethyl cellulose, methylparaben, niacinamide, phenoxyethanol, propylene glycol, propylparaben and purified water.

12 CLINICAL PHARMACOLOGY

12.1 Mechanism of Action

The mechanism of action of metronidazole in the treatment of rosacea is unknown.

12.2 Pharmacodynamics

The pharmacodynamics of metronidazole in association with the treatment of rosacea are unknown.

12.3 Pharmacokinetics

Topical administration of a one gram dose of METROGEL to the face of 13 patients with moderate to severe rosacea once daily for 7 days resulted in a mean ± SD Cmax of metronidazole of 32 ± 9 ng/mL. The mean ± SD AUC(0-24) was 595 ± 154 ng*hr/mL. The mean Cmax and AUC(0-24) are less than 1% of the value reported for a single 250 mg oral dose of metronidazole. The time to maximum plasma concentration (Tmax) was 6-10 hours after topical application.

13 NONCLINICAL TOXICOLOGY

13.1 Carcinogenesis, Mutagenesis, Impairment of Fertility

Metronidazole has shown evidence of carcinogenic activity in a number of studies involving chronic, oral administration in mice and rats, but not in studies involving hamsters.
In several long-term studies in mice, oral doses of approximately 225 mg/m^2/day or greater (approximately 37 times the human topical dose on a mg/m^2 basis) were associated with an increase in pulmonary tumors and lymphomas. Several long-term oral studies in the rat have shown statistically significant increases in mammary and hepatic tumors at doses >885 mg/m^2/day (144 times the human dose).
Metronidazole has shown evidence of mutagenic activity in several in vitro bacterial assay systems. In addition, a dose-related increase in the frequency of micronuclei was observed in mice after intraperitoneal injections. An increase in chromosomal aberrations in peripheral blood lymphocytes was reported in patients with Crohn's disease who were treated with 200 to 1200 mg/day of metronidazole for 1 to 24 months. However, in another study, no increase in chromosomal aberrations in circulating lymphocytes was observed in patients with Crohn's disease treated with the drug for 8 months.
In one published study, using albino hairless mice, intraperitoneal administration of metronidazole at a dose of 45 mg/m^2/day (approximately 7 times the human topical dose on a mg/m^2/day basis) was associated with an increase in ultraviolet radiation-induced skin carcinogenesis. Neither dermal carcinogenicity nor photocarcinogenicity studies have been performed with METROGEL or any marketed metronidazole formulations.

14 CLINICAL STUDIES

In a randomized, vehicle-controlled trial, 746 subjects with rosacea were treated with metronidazole gel, 1% or gel vehicle once daily for 10 weeks. Most subjects had “moderate” rosacea at baseline. Efficacy was determined by recording reduction in inflammatory lesion counts and success rate in the Investigator Global Assessment (percentage of subjects “clear” and “almost clear” of rosacea at the end of the study). The scale is based on the following definitions:

Table 3: Investigator Global Assessment Scale
Score | Grade | Definition
0 | Clear | No signs or symptoms present; at most, mild erythema
1 | Almost Clear | Very mild erythema present. Very few small papules/pustules
2 | Mild | Mild erythema. Several small papules/pustules
3 | Moderate | Moderate erythema. Several small or large papules/pustules, and up to 2 nodules
4 | Severe | Severe erythema. Numerous small and/or large papules/pustules, up to several nodules

The results are shown in the following table:

Table 4: Inflammatory Lesion Counts and Global Scores in a Clinical Trial of Rosacea
 | Metronidazole Gel, 1% |  | Vehicle
 | N | Results N (%) | N | Results N (%)
Inflammatory lesions | 557 |  | 189
Baseline, mean count |  | 18.3 |  | 18.4
Week-10, mean count |  | 8.9 |  | 12.8
Reduction |  | 9.4 (50.7) |  | 5.6 (32.6)
Investigator Global Assessment | 557 |  | 189
Subject clear or almost clear |  | 214 (38.42) |  | 52 (27.51)
Subject with no change |  | 159 (28.5) |  | 77 (40.7)

Subjects treated with metronidazole gel, 1% experienced a mean reduction of 9.4 inflammatory lesions in the Week-10 LOCF group, compared to a reduction of 5.6 for those treated with vehicle, or a difference in means of 3.8 lesions.
The contribution to efficacy of individual components of the vehicle has not been established.

16 HOW SUPPLIED/STORAGE AND HANDLING

METROGEL® a clear, colorless to pale yellow in color, and is supplied as follows:
60 gram tube - NDC 54868-5585-1

Storage Conditions: Store at controlled room temperature: 20˚ to 25˚C (68˚ to 77˚F), excursions permitted between 15˚ and 30˚C (59˚ and 86˚F).

17 PATIENT COUNSELING INFORMATION

Patients using METROGEL should receive the following information and instructions:

1. This medication is to be used as directed.
2. It is for external use only.
3. Avoid contact with the eyes.
4. Cleanse affected area(s) before applying METROGEL.
5. This medication should not be used for any other condition than that for which it is prescribed.
6. Keep out of reach of children.
7. Patients should report any adverse reaction to their physicians.

RX Only

US Patent No. 6,881,726 and 7,348,317

Manufactured by:
G Production Inc.
Baie d'Urfé, Quebec, H9X 3S4 Canada
Made in Canada
Marketed by:
GALDERMA LABORATORIES, L.P.
Fort Worth, Texas 76177 USA

Part Number

Additional barcode labeling by:
Physicians Total Care, Inc.
Tulsa, Oklahoma 74146

PACKAGE LABEL

metrogel 1%
(metronidazole gel), 1%
NDC 54868-5585-1
Rx Only
NET WT. 60 g
GALDERMA
For topical use only. Not for oral, ophthalmic or intravaginal use.
Store at controlled room temperature, 20° - 25°C (68° to 77°F), excursions permitted between 15° - 30°C (59° and 86°F). Keep out of reach of children.
Ususal dosage: Apply a thin film to the entire affected areas after washing once daily in the evening or as directed by the physician. Avoid applicaton close to the eyes.
Each gram contains: 10 mg (1%) metronidazole as active ingredient in a gel base consisting of betadex, edetate disodium, hydroxeyethyl cellulose, methylparaben, niacinamide, phenoxyethanol, propylene glycol, propylparaben, and purified water.
US Patent No. 6,881,726 and 7,348,317